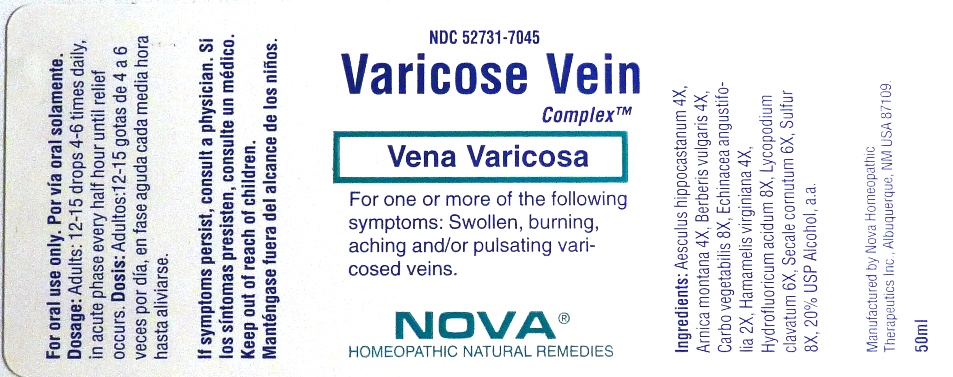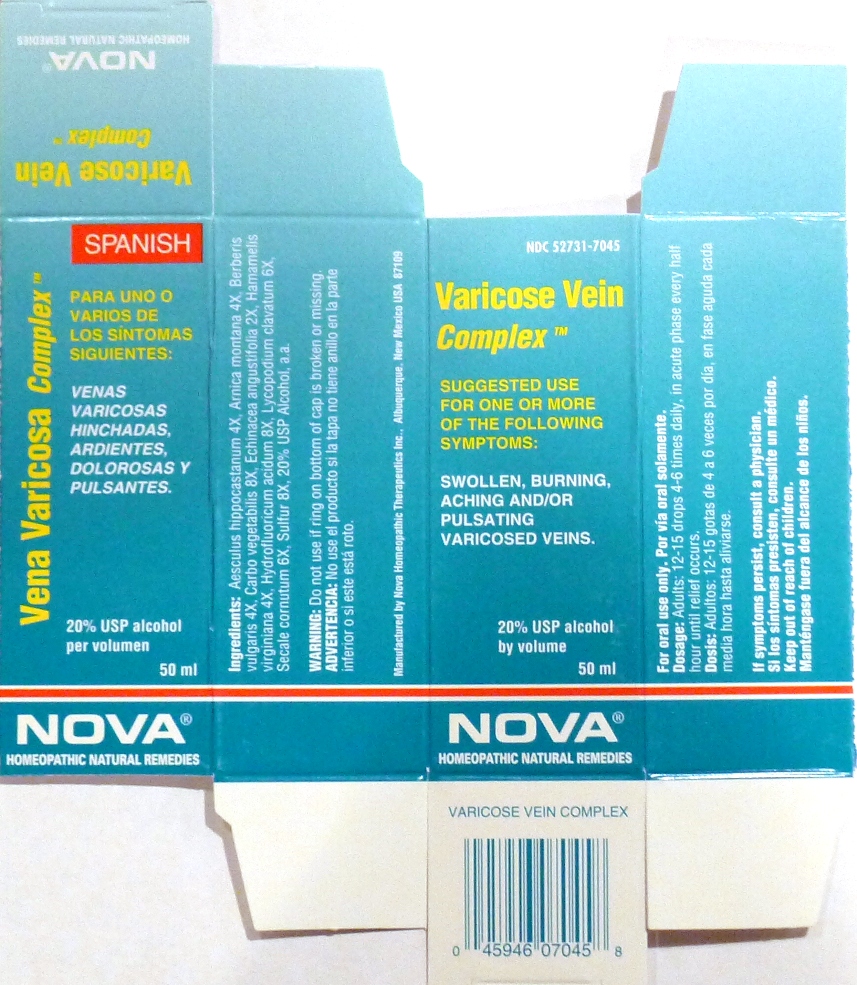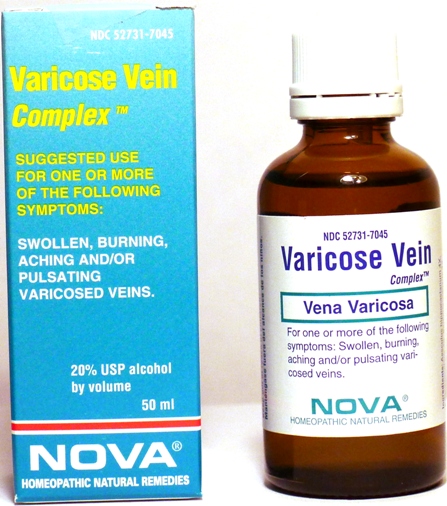 DRUG LABEL: Varicose Vein Complex
NDC: 52731-7045 | Form: LIQUID
Manufacturer: Nova Homeopathic Therapeutics, Inc.
Category: homeopathic | Type: HUMAN OTC DRUG LABEL
Date: 20110601

ACTIVE INGREDIENTS: HORSE CHESTNUT 4 [hp_X]/1 mL; ARNICA MONTANA 4 [hp_X]/1 mL; BERBERIS VULGARIS ROOT BARK 4 [hp_X]/1 mL; ACTIVATED CHARCOAL 8 [hp_X]/1 mL; ECHINACEA ANGUSTIFOLIA 2 [hp_X]/1 mL; HAMAMELIS VIRGINIANA ROOT BARK/STEM BARK 4 [hp_X]/1 mL; HYDROFLUORIC ACID 8 [hp_X]/1 mL; LYCOPODIUM CLAVATUM SPORE 6 [hp_X]/1 mL; CLAVICEPS PURPUREA SCLEROTIUM 6 [hp_X]/1 mL; SULFUR 8 [hp_X]/1 mL
INACTIVE INGREDIENTS: ALCOHOL

Varicose Vein Complex

Purpose:

Suggested use for one or more of the following symptoms:

Swollen, burning, aching and/or pulsating varicosed veins.

Usage and Dosage:

For oral use only.

DOSAGE AND ADMINISTRATION

Adults:
In Acute Phase:
12-15 drops, every half hour until relief occurs
When Relief Occurs:
12-15 drops, 4-6 times per day

Warnings:

Keep out of reach of children.

WARNINGS

If symptoms persist, consult a physician.
Do not use if ring on bottom of cap is broken or missing.

Active Ingredients:

Aesculus hippocastanum 4X, Arnica montana 4X, Berberis vulgaris 4X, Carbo vegetabilis 8X, Echinacea angustifolia 2X, Hamamelis virginiana 4X, Hydrofluoricum acidum 8X, Lycopodium clavatum 6X, Secale cornutum 6X, Sulfur 8X

Inactive Ingredients:

Alcohol, 20% USP

QUESTIONS

Manufactured by Nova Homeopathic Therapeutics Inc., Albuquerque, New Mexico USA 87109
1-800-225-8094

PACKAGE LABEL

Varicose Vein Complex Product

Varicose Vein Complex Bottle Label

Varicose Vein Complex Box